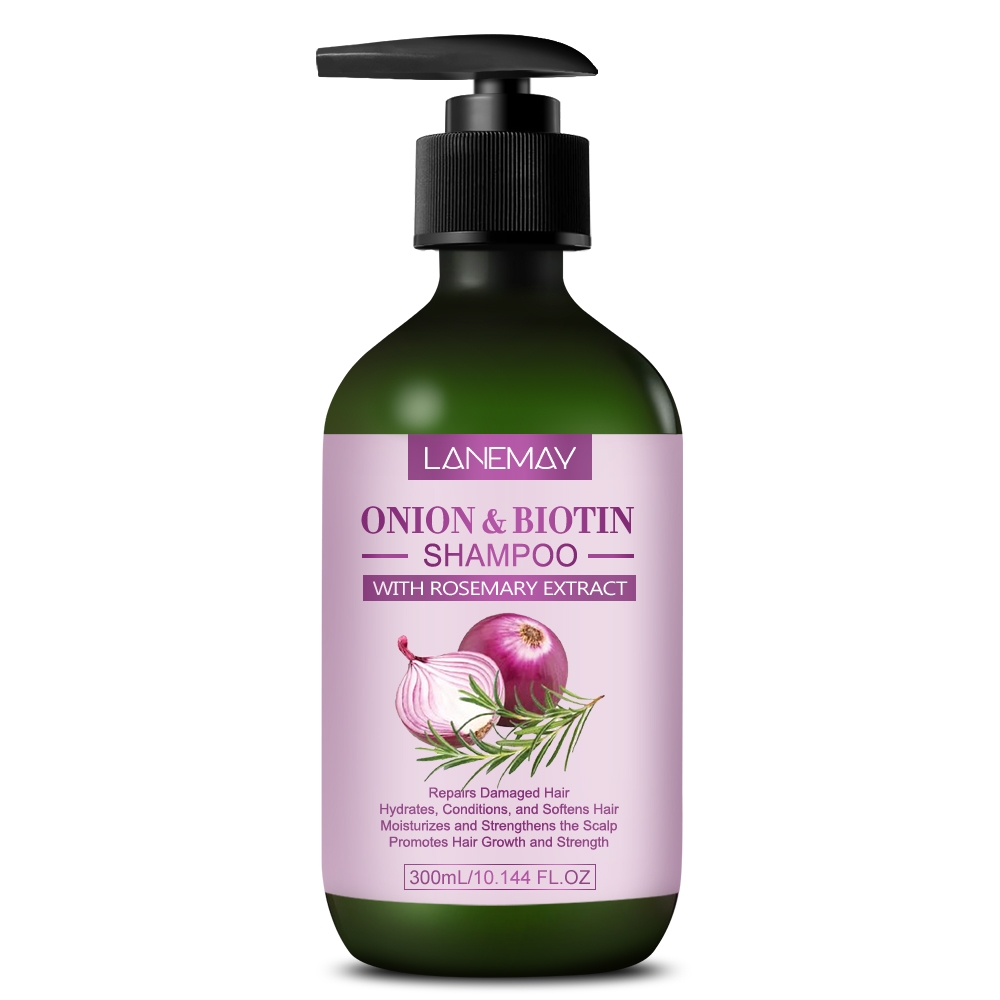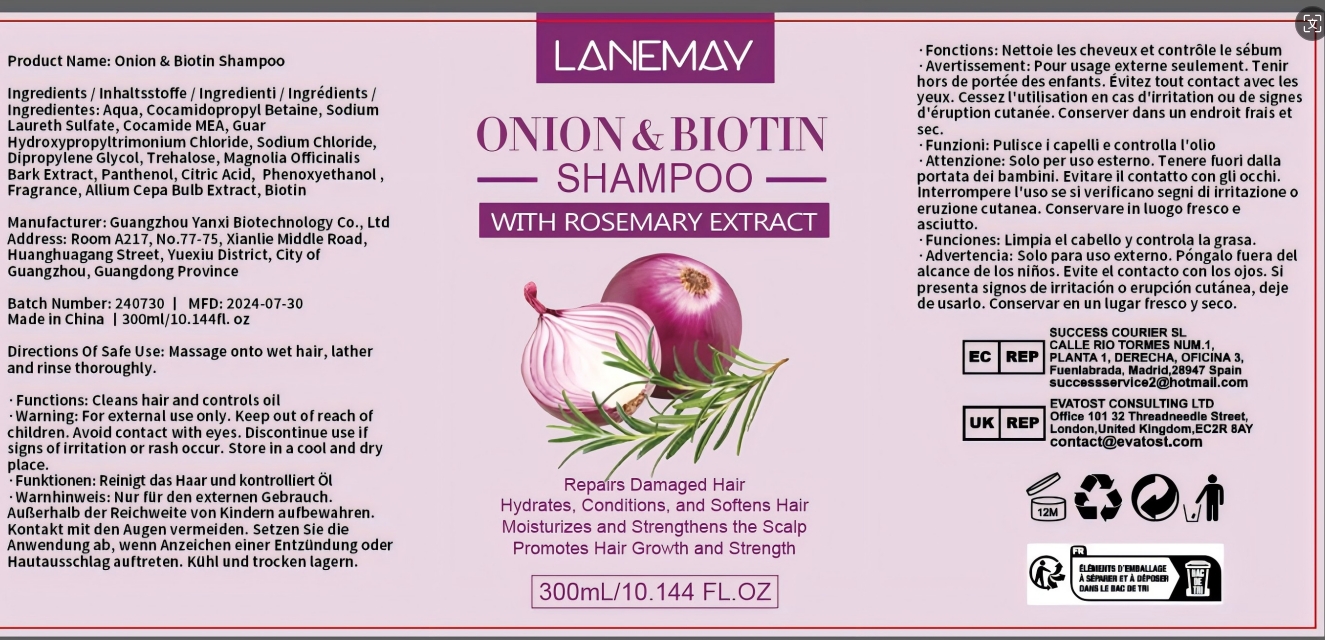 DRUG LABEL: Onion BiotinShampoo
NDC: 84025-147 | Form: SHAMPOO
Manufacturer: Guangzhou Yanxi Biotechnology Co.. Ltd
Category: otc | Type: HUMAN OTC DRUG LABEL
Date: 20240814

ACTIVE INGREDIENTS: COCAMIDOPROPYL BETAINE 5 mg/300 mL; DIPROPYLENE GLYCOL 3 mg/300 mL
INACTIVE INGREDIENTS: WATER

DOSAGE AND ADMINISTRATION

Shampoo for scalp care, relieving dry hair

WARNINGS

Keep out of children

INACTIVE INGREDIENT

Aqua

INDICATIONS AND USAGE

For daily scalp and hair care

Keep out of children

PURPOSE

Relieve hair loss problems and maintain scalp health